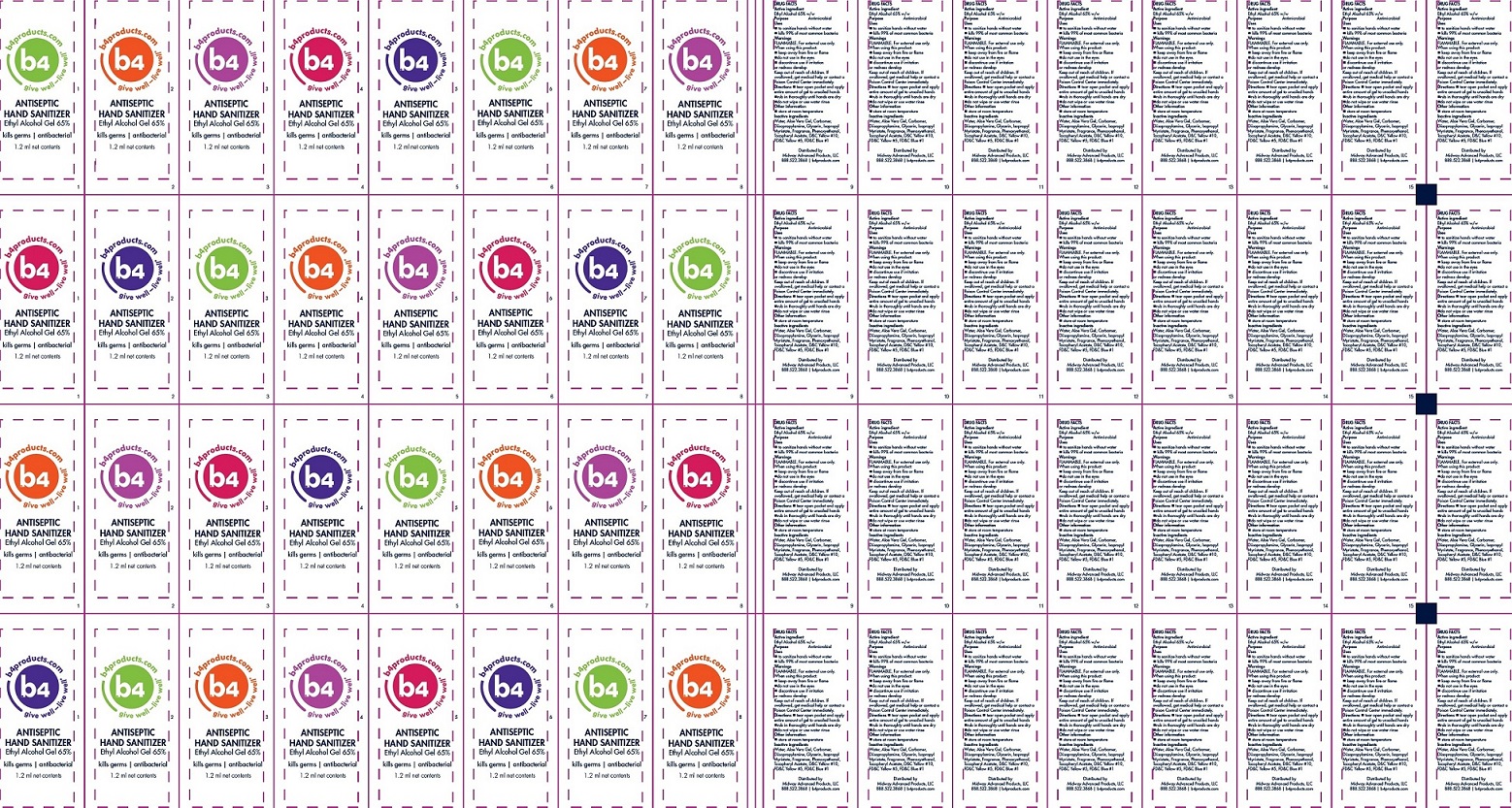 DRUG LABEL: b4 Antiseptic Hand Sanitizer with ethyl alcohol
NDC: 52490-201 | Form: GEL
Manufacturer: Midway Advanced Products, LLC
Category: otc | Type: HUMAN OTC DRUG LABEL
Date: 20180207

ACTIVE INGREDIENTS: ALCOHOL 650 mg/1 mL
INACTIVE INGREDIENTS: WATER; ALOE VERA LEAF; CARBOXYPOLYMETHYLENE; DIISOPROPYLAMINE; GLYCERIN; ISOPROPYL MYRISTATE; PHENOXYETHANOL; .ALPHA.-TOCOPHEROL ACETATE; D&C YELLOW NO. 10; FD&C YELLOW NO. 5; FD&C BLUE NO. 1

b4 Antiseptic Hand Sanitizer with ethyl alcohol gel

Active ingredient

Ethyl Alcohol 65% w/w

Purpose

Antimicrobial

Uses

- to sanitize hands without water
- kills 99% of most common bacteria

Warnings

FLAMMABLE. For external use only.

When using this product:

- keep away from fire or flame
- do not use in eyes
- discontinue use if irritation or redness develop

Keep out of reach of children.

If swallowed, get medical help or contact a Poison Control Center immediately.

Directions

- tear open packet and apply entire amount of gel to unsoiled hands
- rub in thoroughly until hands are dry
- do not wipe or use water rinse

Other information

- store at room temperature

Inactive ingredients

Water, Aloe Vera Gel, Carbomer, Diisopropylamine, Glycerin, Isopropyl Myristate, Fragrance, Phenoxyethanol, Tocopheryl Acetate, D&C Yellow # 10, FD&C Yellow #5, FD&C Blue #1